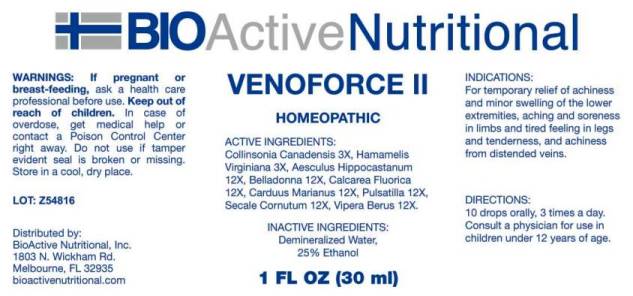 DRUG LABEL: Venoforce
NDC: 43857-0519 | Form: LIQUID
Manufacturer: BioActive Nutritional, Inc.
Category: homeopathic | Type: HUMAN PRESCRIPTION DRUG LABEL
Date: 20241018

ACTIVE INGREDIENTS: COLLINSONIA CANADENSIS ROOT 3 [hp_X]/1 mL; HAMAMELIS VIRGINIANA ROOT BARK/STEM BARK 3 [hp_X]/1 mL; HORSE CHESTNUT 12 [hp_X]/1 mL; ATROPA BELLADONNA 12 [hp_X]/1 mL; CALCIUM FLUORIDE 12 [hp_X]/1 mL; MILK THISTLE 12 [hp_X]/1 mL; PULSATILLA PRATENSIS WHOLE 12 [hp_X]/1 mL; CLAVICEPS PURPUREA SCLEROTIUM 12 [hp_X]/1 mL; VIPERA BERUS VENOM 12 [hp_X]/1 mL
INACTIVE INGREDIENTS: WATER; ALCOHOL

DRUG FACTS:

ACTIVE INGREDIENTS:

Collinsonia Canadensis 3X, Hamamelis Virginiana 3X, Aesculus Hippocastanum 12X, Belladonna 12X, Calcarea Fluorica 12X, Carduus Marianus 12X, Pulsatilla (Pratensis) 12X, Secale Cornutum 12X, Vipera Berus 12X.

INDICATIONS:

For temporary relief of achiness and minor swelling of the lower extremities, aching and soreness in limbs and tired feeling in legs and tenderness, and achiness from distended veins.

WARNINGS:

If pregnant or breast-feeding, ask a health care professional before use.

Keep out of reach of children. In case of overdose, get medical help or contact a Poison Control Center right away.

Do not use if tamper evident seal is broken or missing.

Store in a cool, dry place.

Keep out of reach of children. In case of overdose, get medical help or contact a Poison Control Center right away.

DIRECTIONS:

10 drops orally, 3 times a day. Consult a physician for use in children under 12 years of age.

INDICATIONS:

For temporary relief of achiness and minor swelling of the lower extremities, aching and soreness in limbs and tired feeling in legs and tenderness, and achiness from distended veins.

INACTIVE INGREDIENTS:

Demineralized Water, 25% Ethanol

QUESTIONS:

Distributed by:
BioActive Nutritional, Inc.
1803 N. Wickham Rd.
Melbourne, FL 32935
bioactivenutritional.com

PACKAGE LABEL DISPLAY:

BIOActive Nutritional

VENOFORCE II

HOMEOPATHIC

1 FL OZ (30 ml)